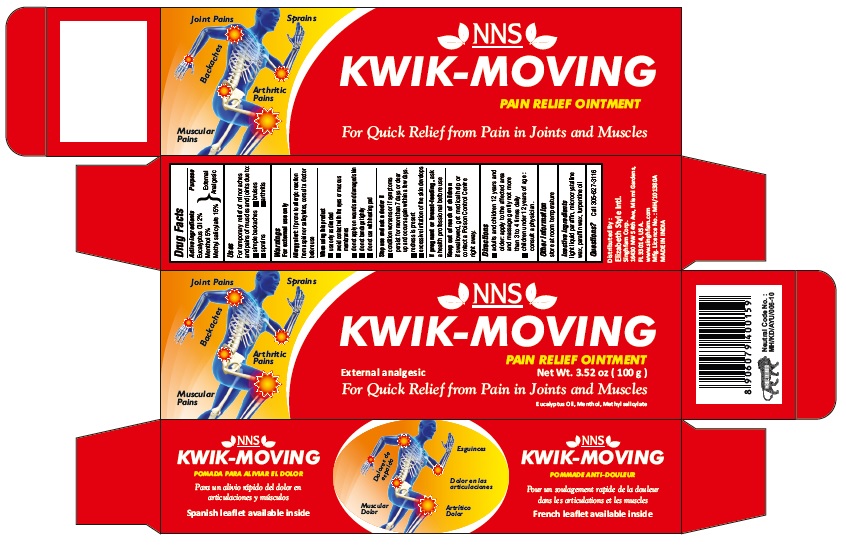 DRUG LABEL: KWIK-MOVING
NDC: 73640-019 | Form: OINTMENT
Manufacturer: N. N. IMPEX
Category: otc | Type: HUMAN OTC DRUG LABEL
Date: 20210219

ACTIVE INGREDIENTS: EUCALYPTUS OIL 2 g/100 g; MENTHOL 5 g/100 g; METHYL SALICYLATE 15 g/100 g
INACTIVE INGREDIENTS: LIGHT MINERAL OIL; MICROCRYSTALLINE WAX; PARAFFIN; TURPENTINE OIL

Active ingredients

Eucalyptus Oil 2% , Menthol 5% ,Methyl salicylate 15%

Purpose

External Analgesic

Warning

For external use only.

Allergy alert:If prone to allergic reaction from aspirin or salicylates, consult a doctor before use.

Stop use and ask a doctor if condition worsens or if symptoms persist for more than 7 days or clear up and occurs again within a few days. Redness is present. Excessive irritation of the skin develops.

When using this product

Use only as directed. Avoid contact with the eyes or mucous membranes. Do not apply on wounds and damaged skin. Do not bandage tightly. Do not use with heating pad.

If pregnant or breast-feeding, ask a health professional before use.

Uses

For temporary relief of minor aches and pains of muscles and joints due to: simple backaches, bruises, sprains, arthritis

Direction

Adults and children 12 years and older: apply to the affected area and massage gently not more than 3 to 4 times daily.
Children under 12 years of age :consult a physician.

Keep out of reach of children

If swallowed, get medical help or contact a Poison Control Center right away.

Inactive Ingredient

Light liquid paraffin, microcrystalline wax, paraffin wax, turpentine oil

Other information

Store at room temperature.